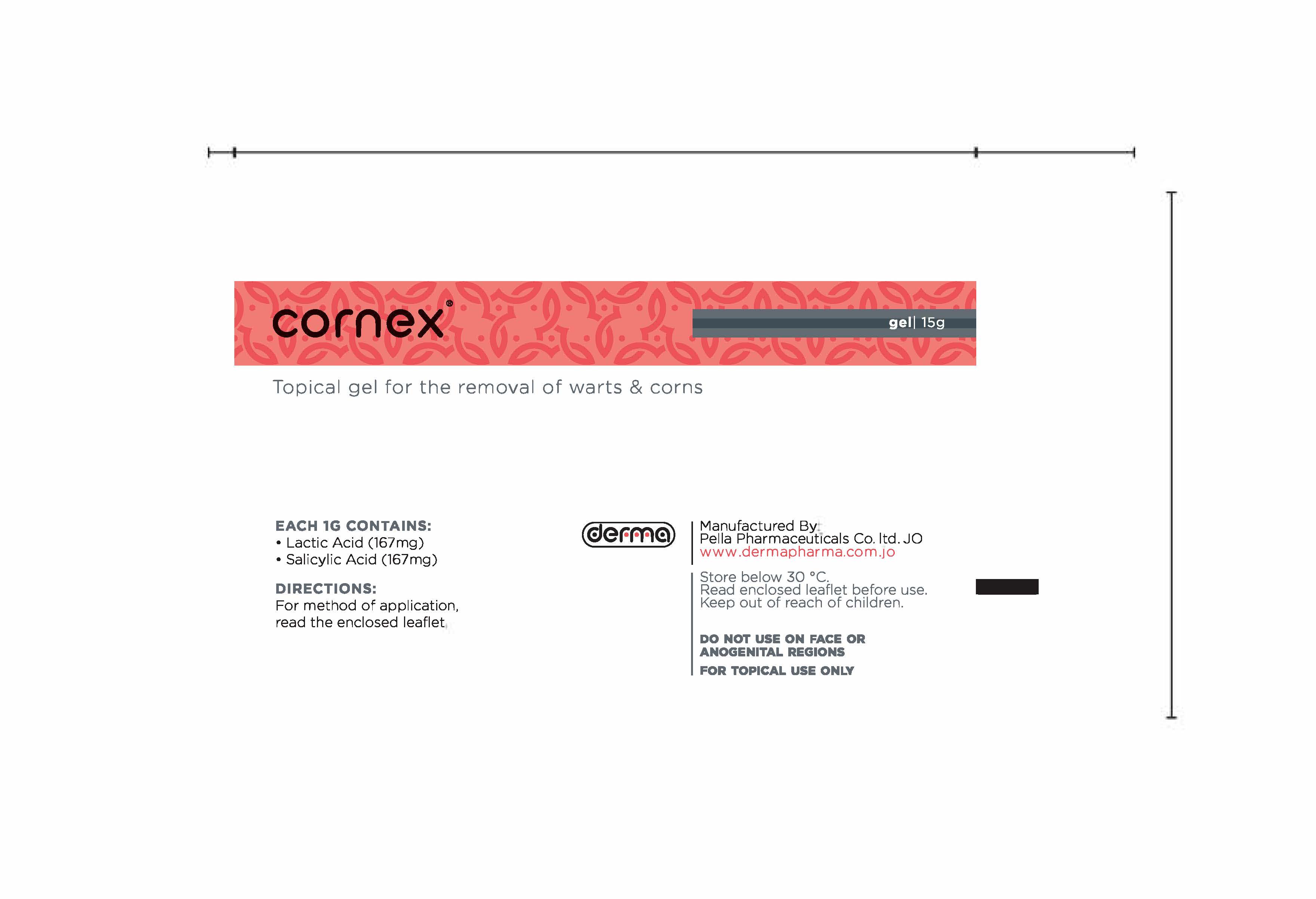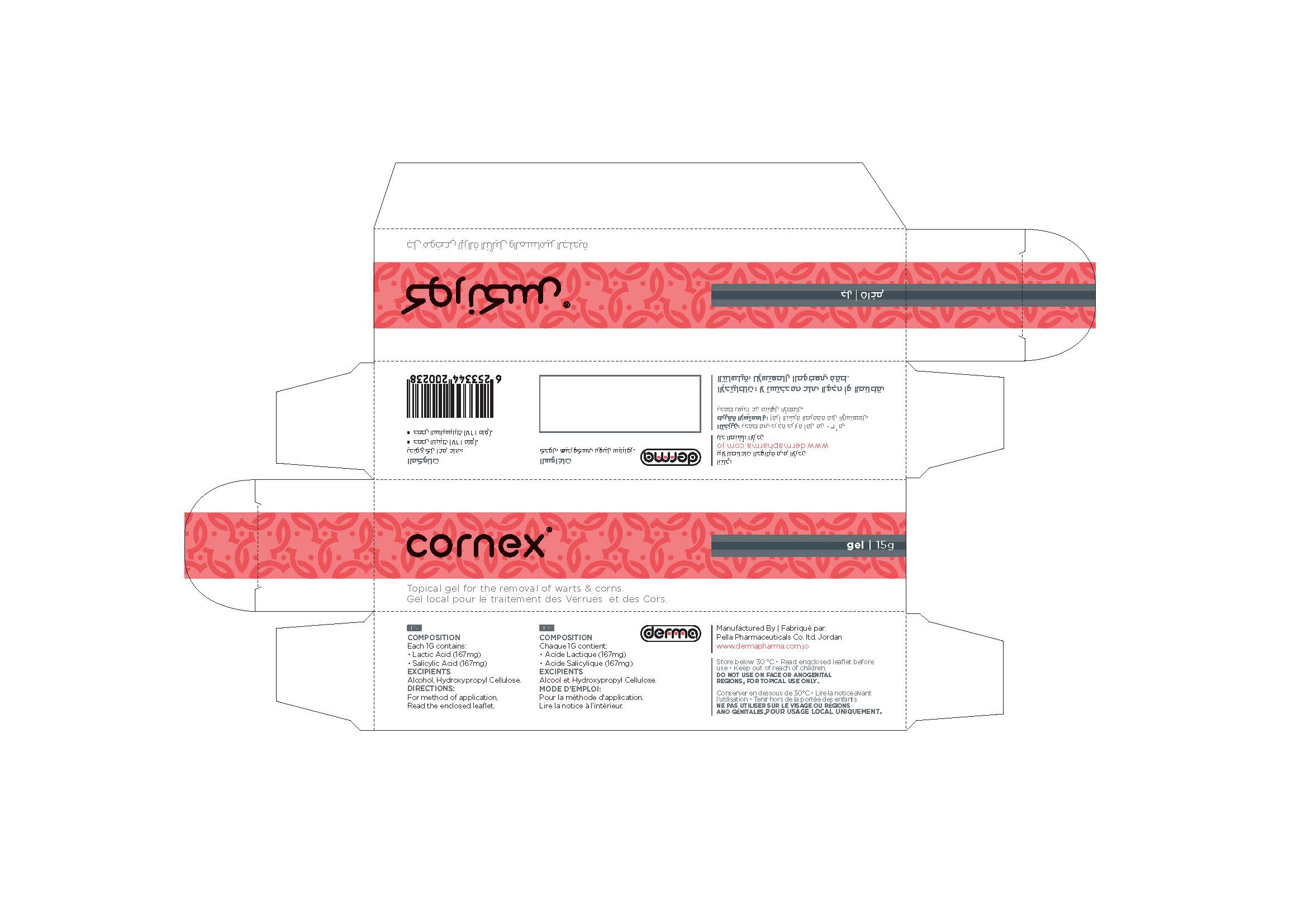 DRUG LABEL: Cornex
NDC: 82160-238 | Form: GEL
Manufacturer: Pella Pharmaceuticals Co. Ltd
Category: otc | Type: HUMAN OTC DRUG LABEL
Date: 20250122

ACTIVE INGREDIENTS: LACTIC ACID 2505 mg/15 g; SALICYLIC ACID 2505 mg/15 g
INACTIVE INGREDIENTS: ALCOHOL; HYDROXYPROPYL CELLULOSE, UNSPECIFIED

Cornex

Active Ingredients

Each one gram contains: Lactic acid 167mg and salicylic acid 167mg.

Composition

Excipients: Alcohol, Hydroxypropyl Cellulose.

Properties

Cornex is a topical gel for the removal of warts and corns.

Indications

Cornex is used to remove Warts and Corns. A wart is a viral infection of the skin surface layer. The incubation period varies from a few weeks to several months. Warts can be spread by contact of the virus with damaged skin, particularly if warm and moist. This is why one of the most common sources of infection is swimming pools. Corns are hard, thick pads of skin caused by pressure and friction. They usually occur on the feet due to poorly fitting shoes. They can also occur on hands. Cornex Gel is suitable for use by adults, children and the elderly.

Contraindications

Cornex is contraindicated in patients with known hypersensitivity to lactic acid and / or salicylic acid or to any other components of this product.
Do not use Cornex if you are diabetic or suffer from poor blood circulation to your hands or feet.

Precautions

Cornex is formulated for the controlled corrosion of keratin and thus care should be taken to apply the product to the wart only. Avoid applying it to normal surrounding skin. Do not use Cornex on the face, mucous membranes or anogenital reagions. Cornex is not recommended for use in infants under 2 years of age. Children under 12 years should only use the product under supervision.

Precaution

As well all the medicines you should keep Cornex out of reach of children.

Drug Interactions

No interaction betyween Lactic acid and Salicylic acid and other drugs or substances are known or suspected.

Warnings

Remember that warts are infectious. To prevent the infection spreading to others always keep to your own towel. Do not walk about barefoot if warts are on the soles of your feet. Be patient, it can take 6 to 12 weeks to completely remove the wart. Do not use Cornex on moles, brithmarks or unusual skin growths or near eyes or on mucous membranes.

Avoid use on broken or inflamed skin.

Dosage and Administration

Remove any plaster and soak the wart in hot water for five minutes. Dry with your own towel. Rub the surface of the warts carefully with a pumice stone or emery board. Apply Cornex daily to the warts. Use only enough Cornex to cover the warts and avoid applying to the surrounding normal skin.

Allow Cornex to dry and cover with plaster if the wart is large or on foot. Continue using Cemex daily until the wart is completely cleared and the ridge lines of the skin have been restored.

Side Effects

Avoid use on large areas of skin; as this may result in absorption of sufficient quantities to cause adverse effects.

Storage

Store below 30 " C.

How supplied

15 g packs.